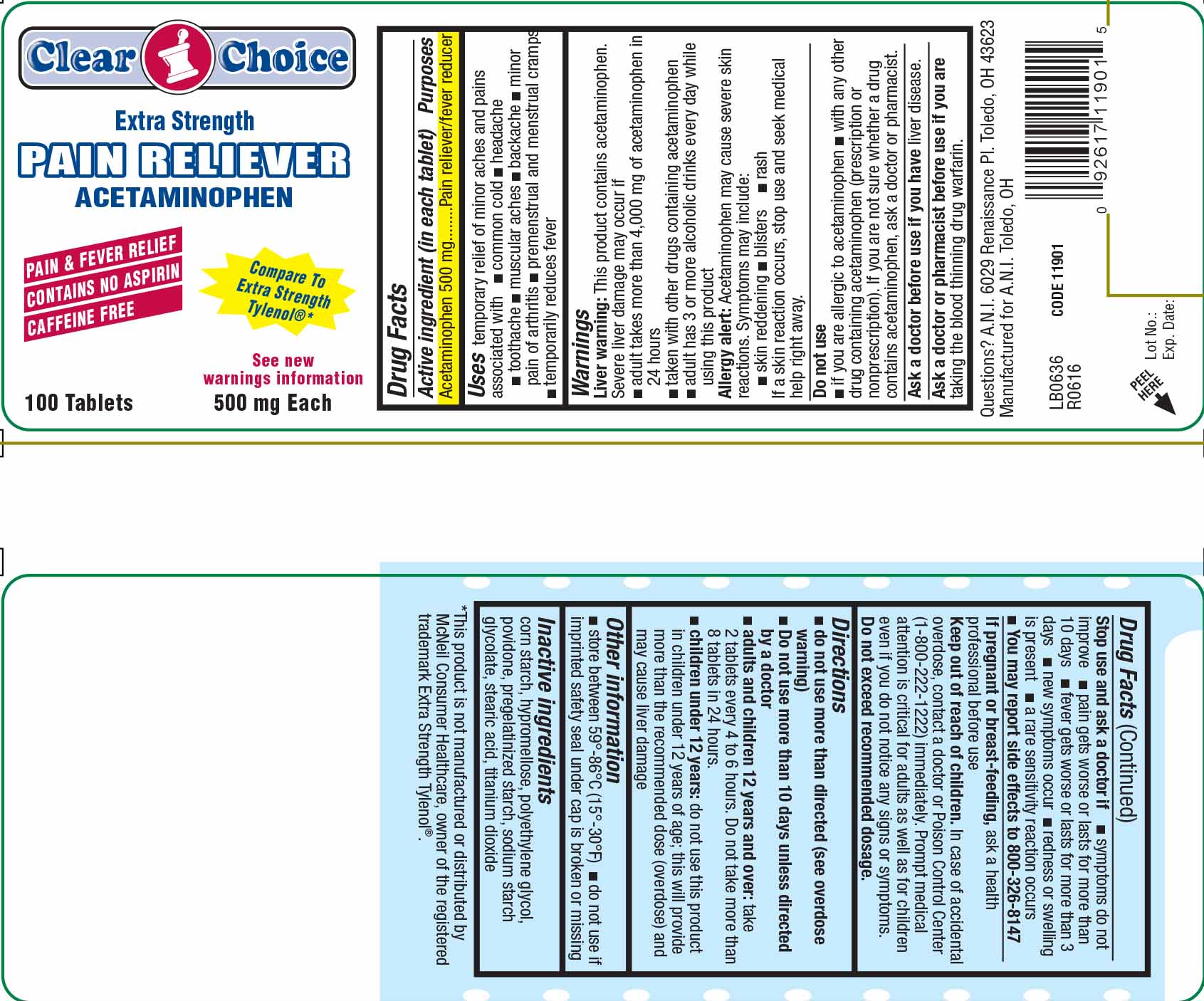 DRUG LABEL: Clear Choice Extra Strength Pain Reliever
NDC: 53185-002 | Form: TABLET
Manufacturer: Athlete's Needs, Inc.
Category: otc | Type: HUMAN OTC DRUG LABEL
Date: 20181211

ACTIVE INGREDIENTS: ACETAMINOPHEN 500 mg/1 1
INACTIVE INGREDIENTS: STARCH, CORN; HYPROMELLOSES; POLYETHYLENE GLYCOL, UNSPECIFIED; STEARIC ACID; TITANIUM DIOXIDE; POVIDONE; SODIUM STARCH GLYCOLATE TYPE A CORN

Clear Choice Extra Strength Pain Reliever

Active Ingredient (in each tablet)

Acetaminophen 500 mg

Purposes

Pain reliever/fever reducer

Uses

temporary relief of minor aches and pains associated with

- common cold
- headache
- toothache
- muscular aches
- backache
- minor pain of arthritis
- premenstrual and menstrual cramps
- temporarily reduces fever

Warnings

Liver warning: This product contains acetaminophen.

- Severe liver damage may occur if
- adult takes more than 4,000mg of acetaminophen in 24 hours
- taken with other drugs containing acetaminophen
- adult has 3 or more alcoholic drinks every day while using this product

Allergy alert: Acetaminophen may cause severe skin reactions.

Symptoms may include:

- skin reddening
- blisters
- rash

If a skin reaction occurs, stop use and seek medical help right away.

Do not use

- if you are allergic to acetaminophen
- with any other drug containing acetaminophen (prescription or nonprescription).

If you are not sure whether a drug contains acetaminophen, ask a doctor or pharmacist.

Ask a doctor before use if you have

liver disease

Ask a doctor or pharmacist before use if you

are taking blood thinning drug warfarin

Stop use and ask a doctor if

- symptoms do not improve
- pain gets worse or lasts for more than 10 days
- fever gets worse or lasts for more than 3 days
- new symptoms occur
- redness or swelling is present
- a rare sensitivity reaction occurs
- You may report side effects to 800-326-8147

If pregnant or breast-feeding,

ask a health professional before use.

Keep out of reach of children.

In case of accidental overdose, contact a doctor or Poison Control Center (1-800-222-1222) immediately.

Prompt medical attention is critical for adults as well as children even if you do not notice any signs or symptoms.

Do not exceed recommended dosage.

Directions

do not use more than directed (see overdose warning)

Do not use more than 10 days unless directed by a doctor

- adults and children 12 years and over: take two tablets every 4 to 6 hours. Do not take more than 8 tablets in 24 hours.
- children under 12 years: do not use this product in children under 12 years of age; this will provide more than the recommended dose (overdose) and may cause liver damage

Other information

- store between 59º-86ºC (15º-30ºF)
- do not use if imprinted safety seal under cap is broken or missing

Inactive ingredients

corn starch, hypromellose, polyethylene glycol, povidone, pregelatinized starch, sodium starch glycolate, stearic acid, titanium dioxide

Package Label

Clear Choice

Extra Strength

PAIN RELIEVER

ACETAMINOPHEN

PAIN & FEVER RELIEF

CONTAINS NO ASPIRIN

CAFFEINE FREE

Compare to Extra Strength Tylenol (R)

See new warnings information

100 Tablets

500 mg Each

Questions? Contact A.N.I. Toledo OH

Manufactured for A.N.I. Toledo OH 436253

Acetaminophen 500mg